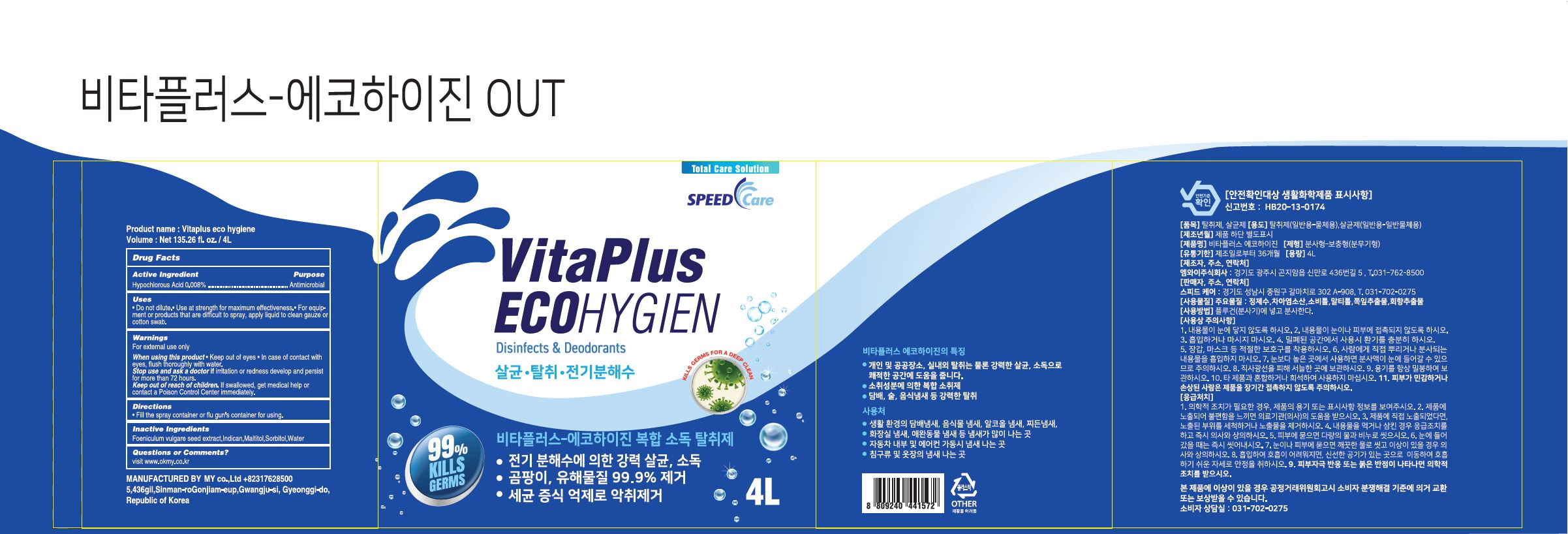 DRUG LABEL: Vitaplus eco hygiene
NDC: 71544-0025 | Form: LIQUID
Manufacturer: MY Corp.,Ltd
Category: otc | Type: HUMAN OTC DRUG LABEL
Date: 20210510

ACTIVE INGREDIENTS: HYPOCHLOROUS ACID 0.008 g/100 mL
INACTIVE INGREDIENTS: INDICAN; SORBITOL; MALTITOL; WATER; FENNEL SEED

ACTIVE INGREDIENT

hypochlorous acid

INACTIVE INGREDIENT

Foeniculum vulgare seed extract, Indican, Maltitol, Sorbitol, Water

PURPOSE

Antiseptic

keep out of reach of the children

INDICATIONS AND USAGE

Do not dilute.• Use at strength for maximum effectiveness.• For equipment or products that are difficult to spray, apply liquid to clean gauze or cotton swab.

Warnings

For external use only.

When using this product • Keep out of eyes • In case of contact with eyes, flush thoroughly with water.

Stop use and ask a doctor ifirritation or redness develop and persist for more than 72 hours.

Keep out of reach of children. If swallowed, get medical help or contact a Poison Control Center immediately.

DOSAGE AND ADMINISTRATION

for external use only